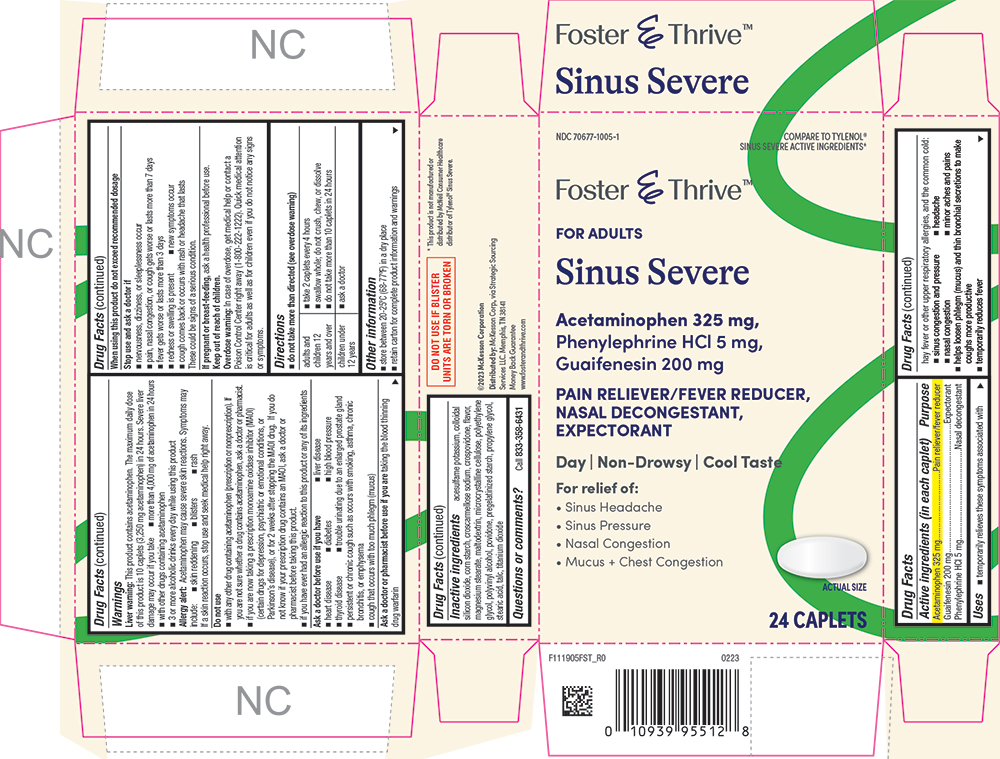 DRUG LABEL: Sinus Severe
NDC: 70677-1005 | Form: TABLET, COATED
Manufacturer: STRATEGIC SOURCING SERVICES LLC
Category: otc | Type: HUMAN OTC DRUG LABEL
Date: 20251209

ACTIVE INGREDIENTS: ACETAMINOPHEN 325 mg/1 1; GUAIFENESIN 200 mg/1 1; PHENYLEPHRINE HYDROCHLORIDE 5 mg/1 1
INACTIVE INGREDIENTS: ACESULFAME POTASSIUM; SILICON DIOXIDE; CROSCARMELLOSE SODIUM; CROSPOVIDONE; MAGNESIUM STEARATE; MALTODEXTRIN; CELLULOSE, MICROCRYSTALLINE; POLYETHYLENE GLYCOL, UNSPECIFIED; POLYVINYL ALCOHOL; POVIDONE; STARCH, PREGELATINIZED CORN; PROPYLENE GLYCOL; STEARIC ACID; TALC; TITANIUM DIOXIDE

1119-FST-2023-0425

Drug Facts

ACTIVE INGREDIENT

Active ingredients (in each caplet) | Purpose
Acetaminophen 325 mg | Pain reliever/fever reducer
Guaifenesin 200 mg | Expectorant
Phenylephrine HCl 5 mg | Nasal decongestant

Uses

- temporarily relieves these symptoms associated with hay fever or other upper respiratory allergies, and the common cold:
  - sinus congestion and pressure
  - headache
  - nasal congestion
  - minor aches and pains
- helps loosen phlegm (mucus) and thin bronchial secretions to make coughs more productive
- temporarily reduces fever

Warnings

Liver warning

This product contains acetaminophen. The maximum daily dose of this product is 10 caplets (3,250 mg acetaminophen) in 24 hours. Severe liver damage may occur if you take

- more than 4,000 mg of acetaminophen in 24 hours
- with other drugs containing acetaminophen
- 3 or more alcoholic drinks every day while using this product

Allergy alert

Acetaminophen may cause severe skin reactions. Symptoms may include:

- skin reddening
- blisters
- rash

If a skin reaction occurs, stop use and seek medical help right away.

Do not use

- with any other drug containing acetaminophen (prescription or nonprescription). If you are not sure whether a drug contains acetaminophen, ask a doctor or pharmacist.
- if you are now taking a prescription monoamine oxidase inhibitor (MAOI) (certain drugs for depression, psychiatric, or emotional conditions, or Parkinson's disease), or for 2 weeks after stopping the MAOI drug. If you do not know if your prescription drug contains an MAOI, ask a doctor or pharmacist before taking this product.
- if you have ever had an allergic reaction to this product or any of its ingredients

Ask a doctor before use if you have

- liver disease
- heart disease
- high blood pressure
- thyroid disease
- diabetes
- trouble urinating due to an enlarged prostate gland
- persistent or chronic cough such as occurs with smoking, asthma, chronic bronchitis, or emphysema
- cough that occurs with too much phlegm (mucus)

Ask a doctor or pharmacist before use if you are taking the blood thinning drug warfarin

When using this product do not exceed recommended dosage

Stop use and ask a doctor if

- nervousness, dizziness, or sleeplessness occur
- pain, nasal congestion, or cough gets worse or lasts more than 7 days
- fever gets worse or lasts more than 3 days
- redness or swelling is present
- new symptoms occur
- cough comes back or occurs with rash or headache that lasts

These could be signs of a serious condition.

PREGNANCY OR BREAST FEEDING

If pregnant or breast-feeding, ask a health professional before use.

Overdose warning

In case of overdose, get medical help or contact a Poison Control Center right away (1-800-222-1222). Quick medical attention is critical for adults as well as for children even if you do not notice any signs or symptoms.

Directions

- do not take more than directed (see overdose warning)

adults and children 12 years and over | - take 2 caplets every 4 hours - swallow whole – do not crush, chew, or dissolve - do not take more than 10 caplets in 24 hours
children under 12 years | - ask a doctor

Other information

- store between 20-25ºC (68-77ºF) in a dry place
- retain carton for complete product information and warnings

Inactive ingredients

acesulfame potassium, colloidal silicon dioxide, corn starch, croscarmellose sodium, crospovidone, flavor, magnesium stearate, maltodextrin, microcrystalline cellulose, polyethylene glycol, polyvinyl alcohol, povidone, pregelatinized starch, propylene glycol, stearic acid, talc, titanium dioxide

Questions or comments?

Call 833-358-6431

PRINCIPAL DISPLAY PANEL

NDC 70677-1005-1

COMPARE TO TYLENOL® SINUS SEVERE ACTIVE INGREDIENTS*

Foster & Thrive™

FOR ADULTS

Sinus Severe

Acetaminophen 325 mg,

Phenylephrine HCl 325 mg,

Guaifenesin 200 mg

PAIN RELIEVER/FEVER REDUCER,

NASAL DECONGESTANT,

EXPECTORANT

Day | Non-Drowsy | Cool Taste

For relief of:

• Sinus Headache

• Sinus Pressure

• Nasal Congestion

• Mucus + Chest Congestion

ACTUAL SIZE

24 CAPLETS